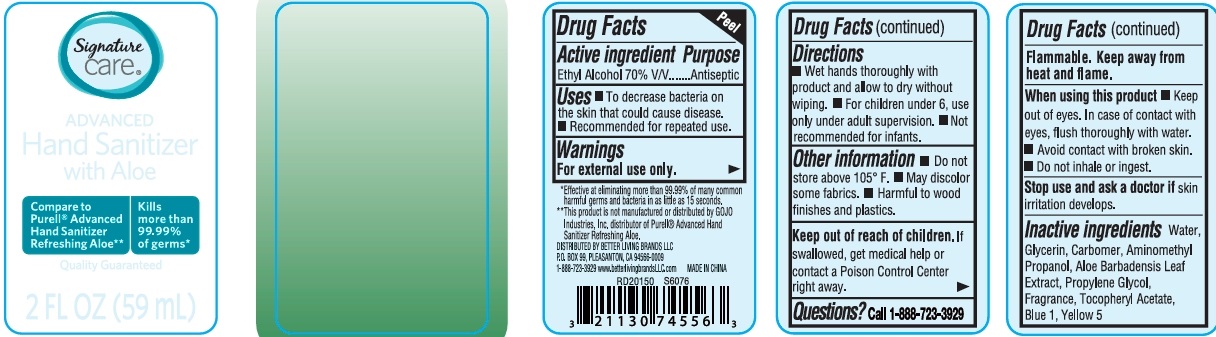 DRUG LABEL: Signature Care Advanced Hand Sanitizer With Aloe
NDC: 74149-107 | Form: GEL
Manufacturer: Yiwu Yangjie Daily Chemicals Co.,Ltd.
Category: otc | Type: HUMAN OTC DRUG LABEL
Date: 20250516

ACTIVE INGREDIENTS: ALCOHOL 70 mL/100 mL
INACTIVE INGREDIENTS: WATER; PROPYLENE GLYCOL; GLYCERIN; .ALPHA.-TOCOPHEROL ACETATE; AMINOMETHYLPROPANOL; TROLAMINE; ALOE BARBADENSIS LEAF JUICE; BLUE 1; YELLOW 5

Drug Facts

Active ingredient Ethyl Alcohol ........... 70%

PURPOSE

Antiseptic

KEEP OUT OF REACH OF CHILDREN

If swallowed, get medical help or contact a poison control center right away.

INDICATIONS AND USAGE

- To decrease bacteria on the skin that could cause disease.
- recommended for repeated use

WARNINGS

For external use only

Flammable. Keep away from heat or flame.

When using this product

- Keep out of eyes. In case of contact with eyes, flush thoroughly with water.
- Avoid contact with broken skin.
- Do not inhale or ingest.

DOSAGE AND ADMINISTRATION

- wet hands thoroughly with product and allow to dry without wiping.
- For children under 6, use only under adult supervision.
- Not recommended for infants.

INACTIVE INGREDIENT

Water, Glycerin, Carbomer, Aminomethyl Propanol, Aloe Barbadensis Leaf Extract, Propylene Glycol, Fragrance, Tocopheryl Acetate, blue 1, yellow 5